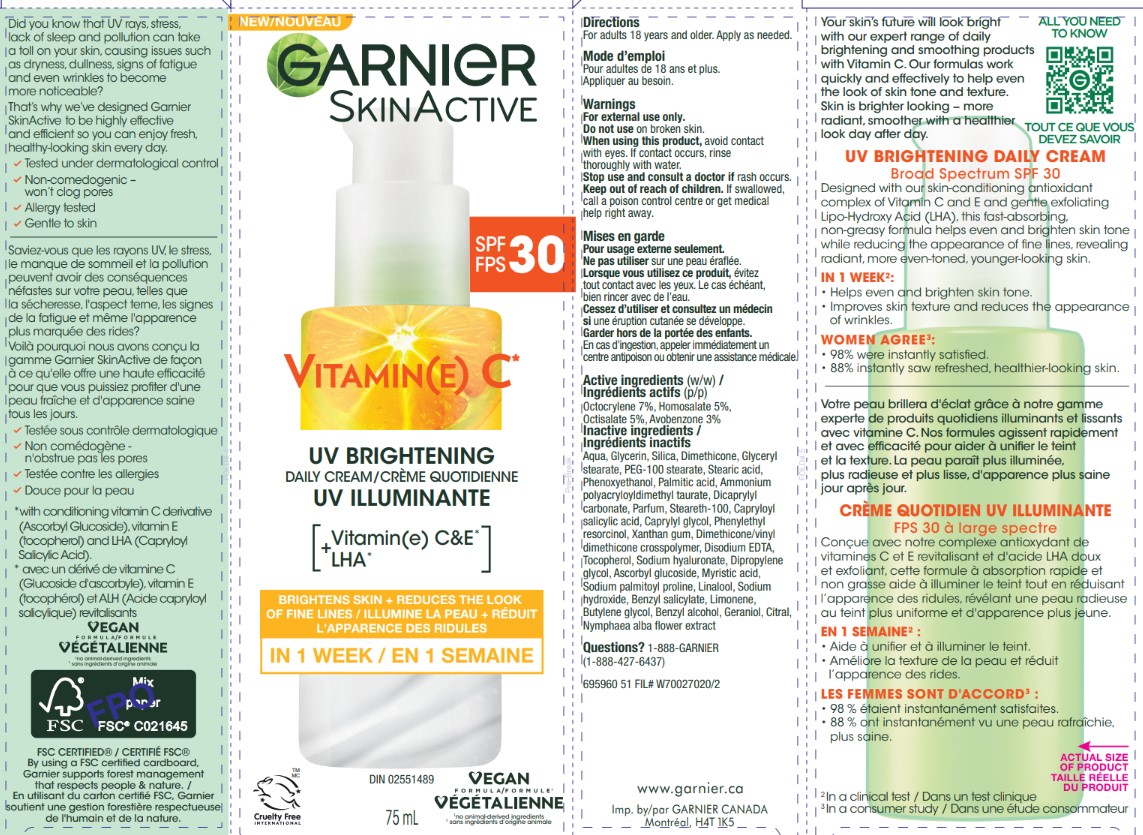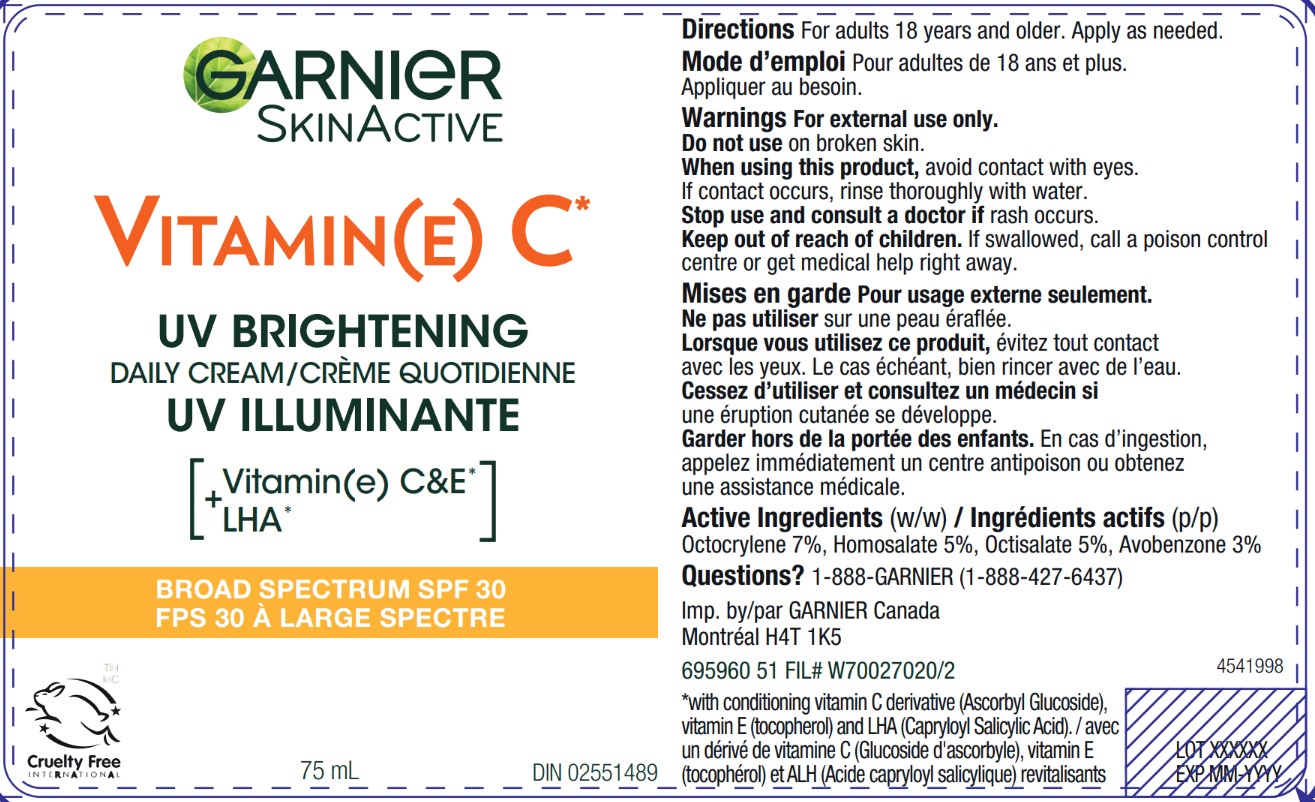 DRUG LABEL: Garnier SkinActive Vitamin(E) C UV Brightening Daily Broad Spectrum SPF 30
NDC: 49967-607 | Form: CREAM
Manufacturer: L’Oreal USA Products Inc
Category: otc | Type: HUMAN OTC DRUG LABEL
Date: 20260107

ACTIVE INGREDIENTS: OCTOCRYLENE 70 mg/1 mL; HOMOSALATE 50 mg/1 mL; OCTISALATE 50 mg/1 mL; AVOBENZONE 30 mg/1 mL
INACTIVE INGREDIENTS: AQUA; GLYCERIN; SILICA; DIMETHICONE; GLYCERYL STEARATE; PEG-100 STEARATE; STEARIC ACID; PHENOXYETHANOL; PALMITIC ACID; AMMONIUM POLYACRYLOYLDIMETHYL TAURATE; DICAPRYLYL CARBONATE; STEARETH-100; CAPRYLOYL SALICYLIC ACID; CAPRYLYL GLYCOL; PHENYLETHYL RESORCINOL; XANTHAN GUM; DIMETHICONE/VINYL DIMETHICONE CROSSPOLYMER (HARD PARTICLE); DISODIUM EDTA-COPPER; TOCOPHEROL; SODIUM HYALURONATE; DIPROPYLENE GLYCOL; ASCORBYL GLUCOSIDE; MYRISTIC ACID; SODIUM PALMITOYL PROLINE; LINALOOL; SODIUM HYDROXIDE; BENZYL SALICYLATE; LIMONENE, (+)-; BUTYLENE GLYCOL; BENZYL ALCOHOL; GERANIOL; CITRAL; NYMPHAEA ALBA FLOWER

Drug Facts

Directions

For adults 18 years and older. Apply as needed.

Warnings

For external use only.

Do not use

on broken skin.

When using

this product, avoid contact with eyes. If contact occurs, rinse thoroughly with water.

Stop use

and consult a doctor if rash occurs.

Keep out of reach of children.

If swallowed, call a poison control centre or get medical help right away.

Active ingredients (w/w)

Octocrylene 7%, Homosalate 5%, Octisalate 5%, Avobenzone 3%

Inactive ingredients

Aqua, Glycerin, Silica, Dimethicone, Glyceryl stearate, PEG-100 stearate, Stearic acid, Phenoxyethanol, Palmitic acid, Ammonium polyacryloyldimethyl taurate, Dicaprylyl carbonate, Parfum, Steareth-100, Capryloyl salicylic acid, Caprylyl glycol, Phenylethyl resorcinol, Xanthan gum, Dimethicone/vinyl dimethicone crosspolymer, Disodium EDTA, Tocopherol, Sodium hyaluronate, Dipropylene glycol, Ascorbyl glucoside, Myristic acid, Sodium palmitoyl proline, Linalool, Sodium hydroxide, Benzyl salicylate, Limonene, Butylene glycol, Benzyl alcohol, Geraniol, Citral, Nymphaea alba flower extract

Questions?

1-888-GARNIER (1-888-427-GARNIER)